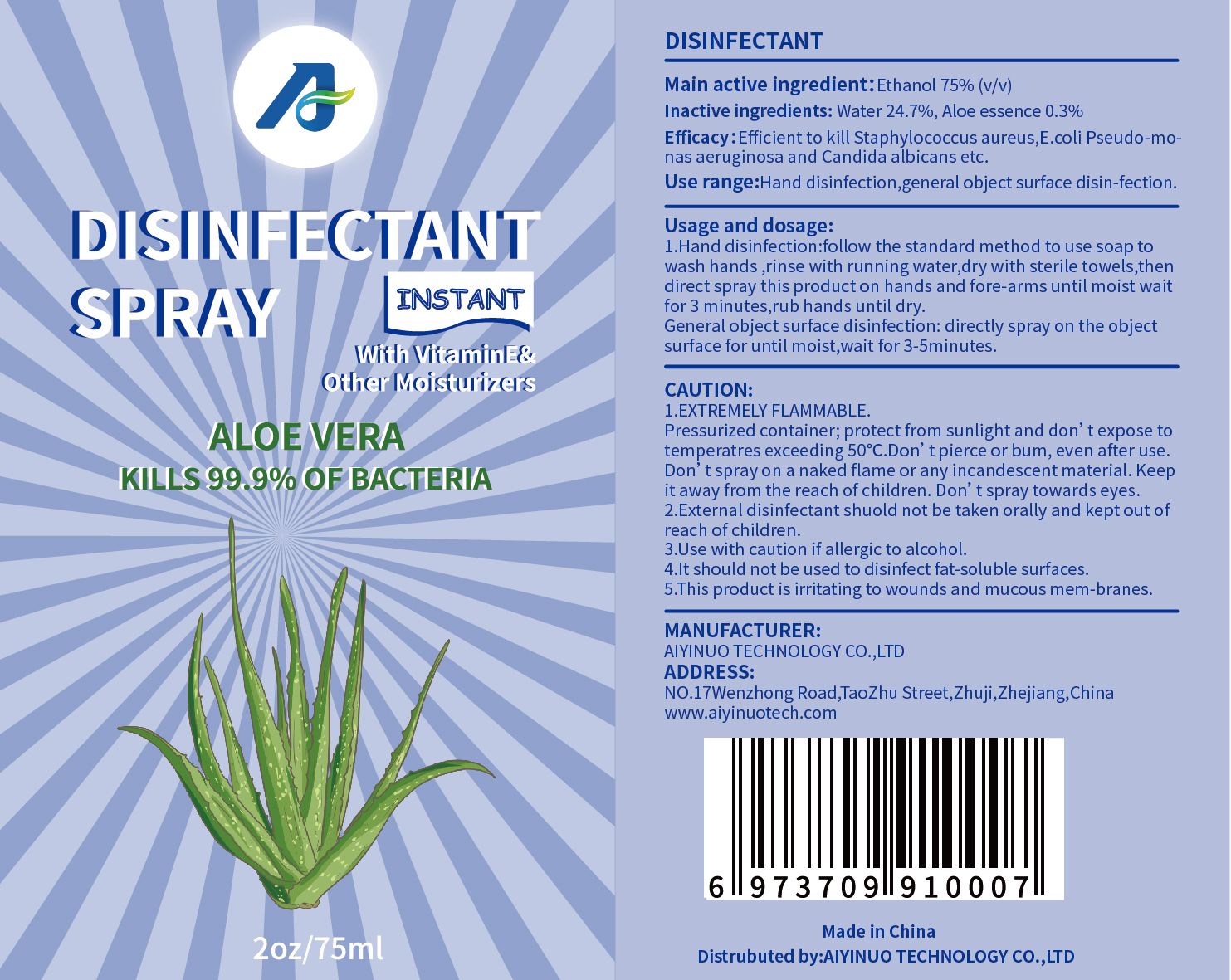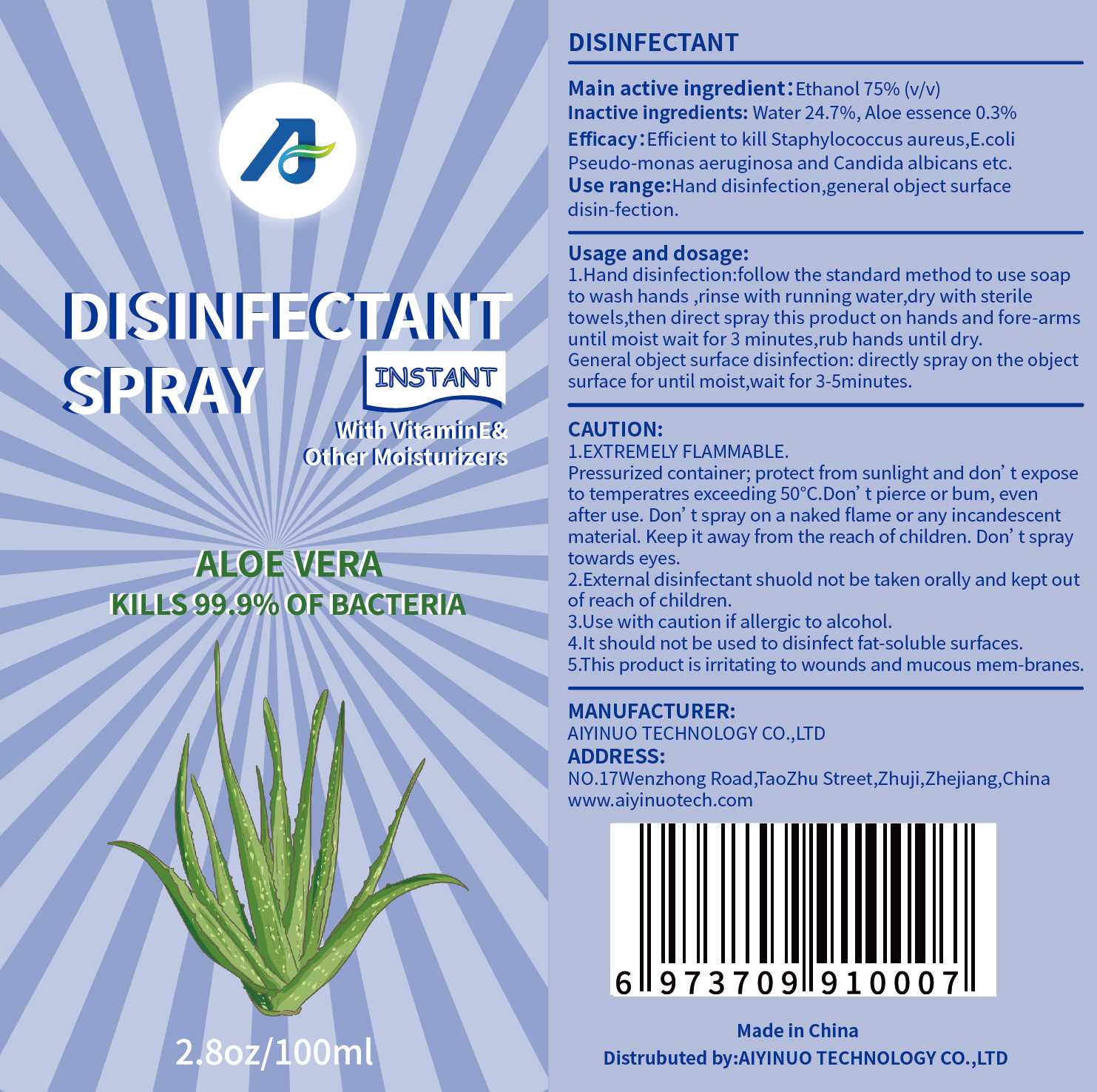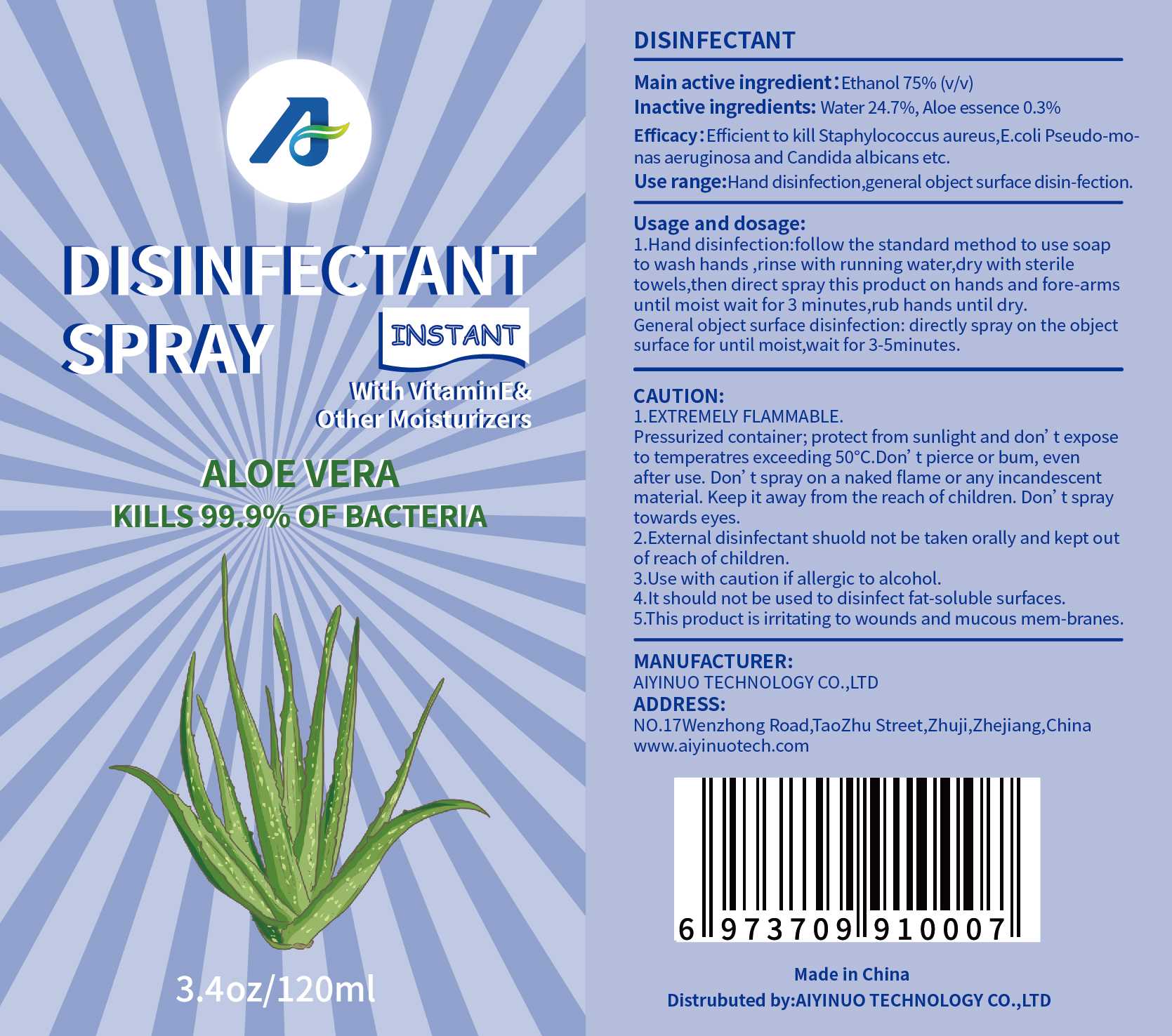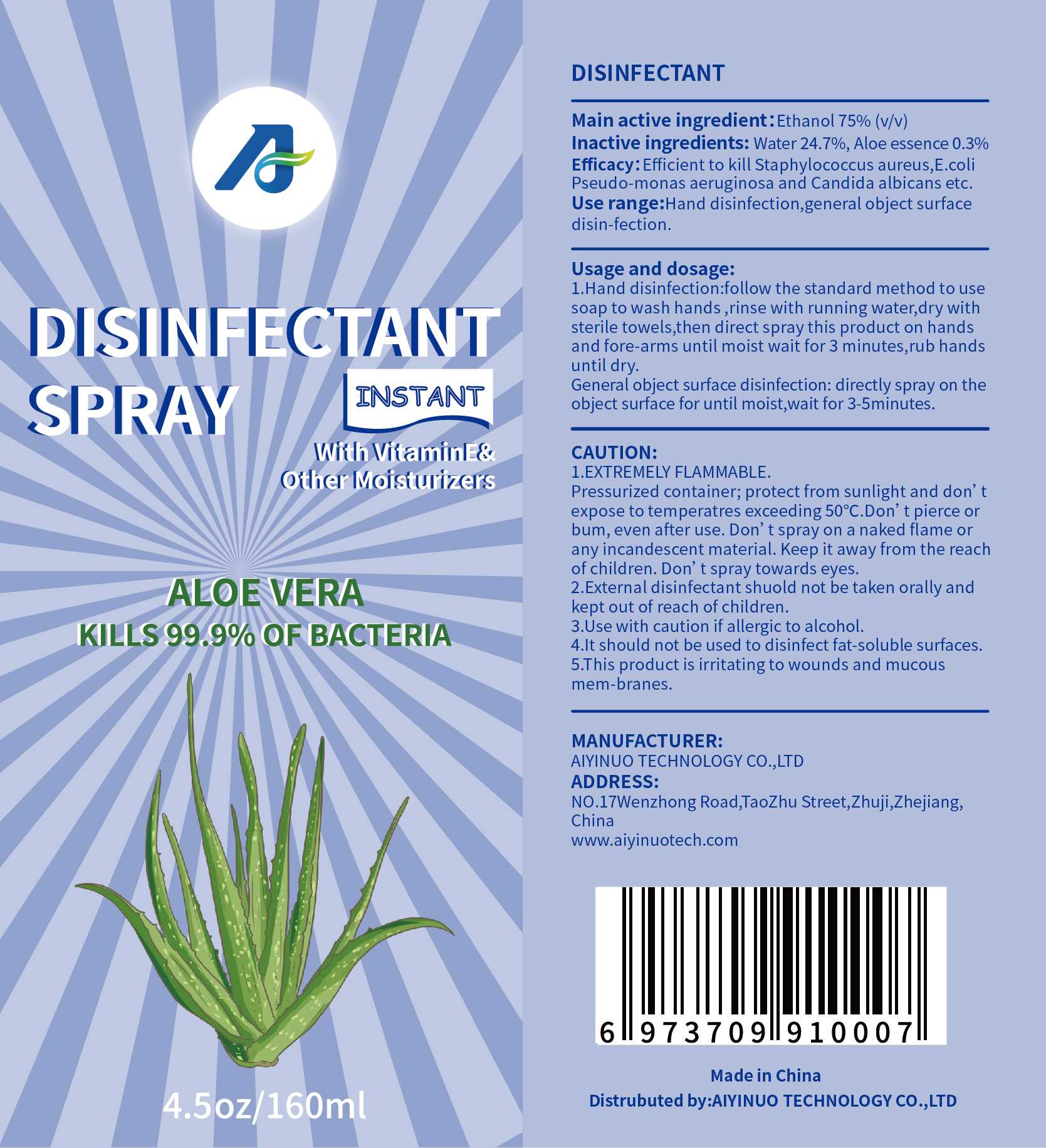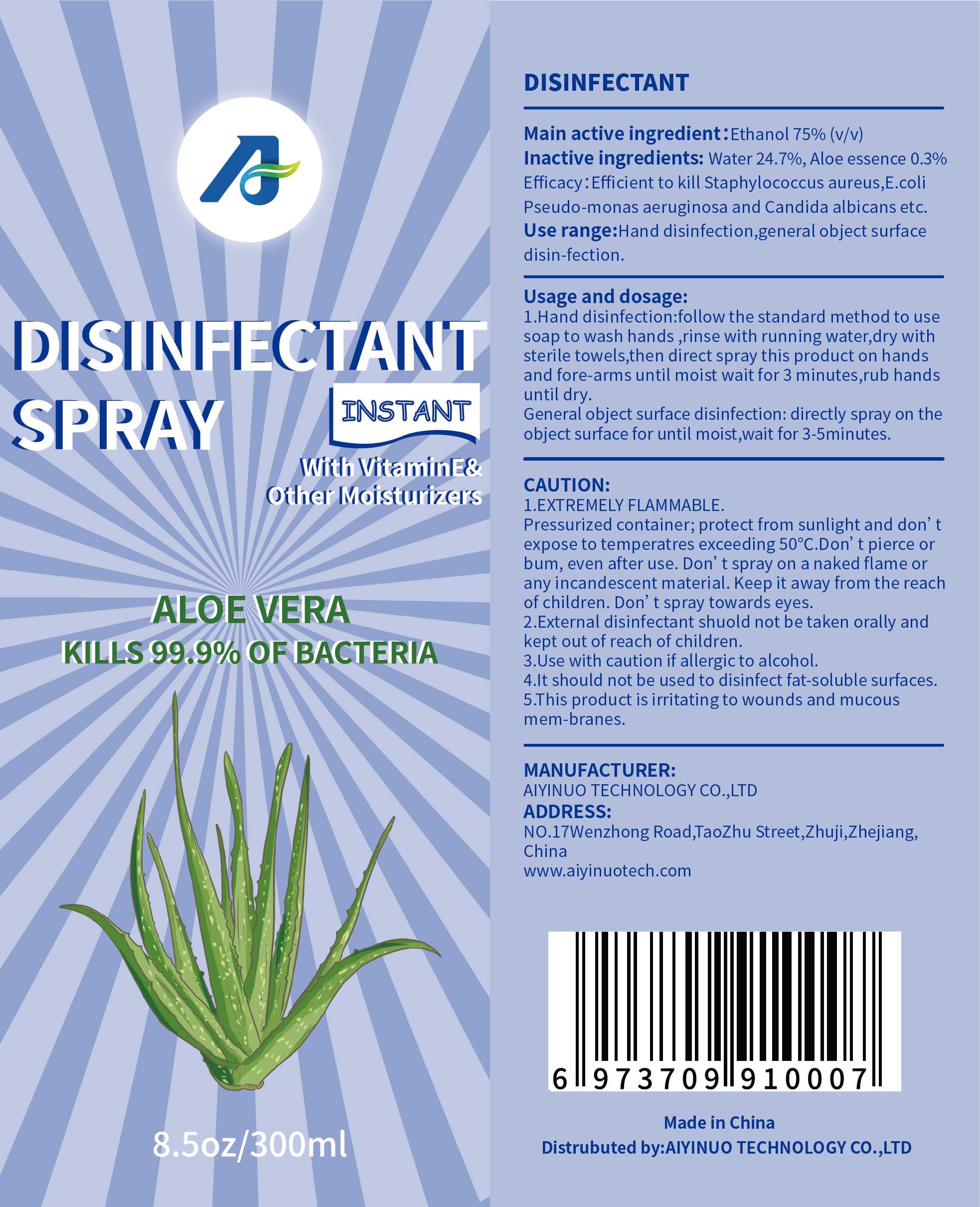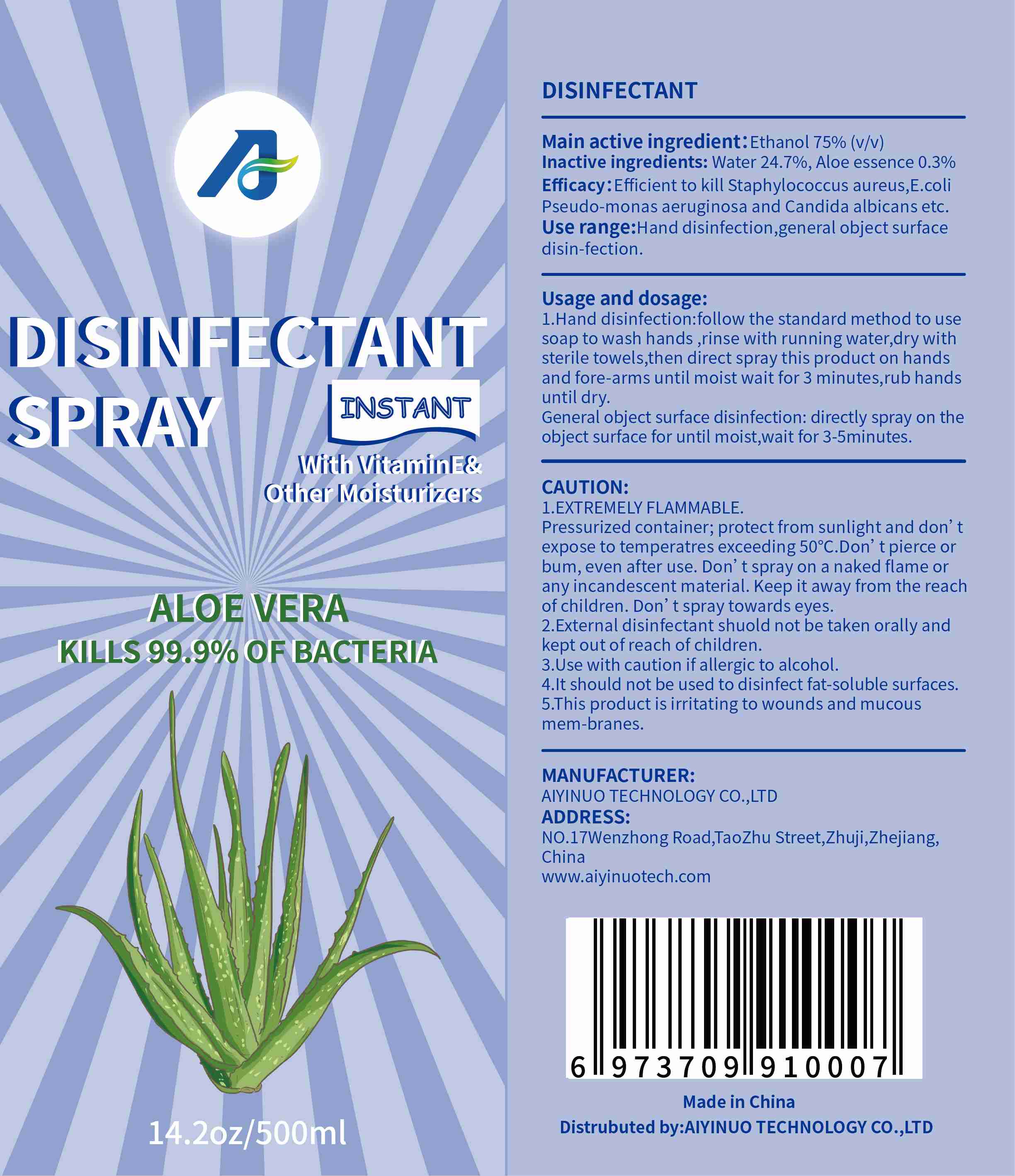 DRUG LABEL: DISINFECTANT
NDC: 80598-001 | Form: SPRAY
Manufacturer: Aiyinuo Technology Co., Ltd.
Category: otc | Type: HUMAN OTC DRUG LABEL
Date: 20200924

ACTIVE INGREDIENTS: ALCOHOL 75 mL/100 mL
INACTIVE INGREDIENTS: ALOE; WATER

80598-001
DISINFECTANT SPRAY

Active Ingredient(s)

Ethanol 75%(v/v)

Purpose

Efficient to kill Staphylococcus aureus,E.coli Pseudo-monas aeruginosa and Candida albicans etc.

Use

Hand disinfection,general object surface disin-fection.

Warnings

l.EXTREMELY FLAMMABLE.
Pressurized container; protect from sunlight and don't expose to temperatres exceeding S0°C.Don' t pierce or bum, even after use. Don't spray on a naked flame or any incandescent material. Keep it away from the reach of children. Don't spray towards eyes.
2.External disinfectant shuold not be taken orally and kept out of reach of children.
3.Use with caution if allergic to alcohol.
4.lt should not be used to disinfect fat-soluble surfaces.
5.This product is irritating to wounds and mucous mem-branes.

Do not use

Pressurized container; protect from sunlight and don't expose to temperatres exceeding S0°C.Don' t pierce or bum, even after use. Don't spray on a naked flame or any incandescent material. Keep it away from the reach of children. Don't spray towards eyes.

WHEN USING

External disinfectant shuold not be taken orally and kept out of reach of children.
Use with caution if allergic to alcohol.
lt should not be used to disinfect fat-soluble surfaces.
This product is irritating to wounds and mucous mem-branes.

STOP USE

/

KEEP OUT OF REACH OF CHILDREN

External disinfectant shuold not be taken orally and kept out of reach of children.

Directions

l.Hand disinfection:follow the standard method to use soap to wash hands ,rinse with running water,dry with sterile towels,then direct spray this product on hands and fore-arms until moist wait for 3 minutes,rub hands until dry.
General object surface disinfection: directly spray on the object surface for until moist,wait for 3-Sminutes.

Other information

/

Inactive ingredients

Water 24.7%, Aloe essence 0.3%